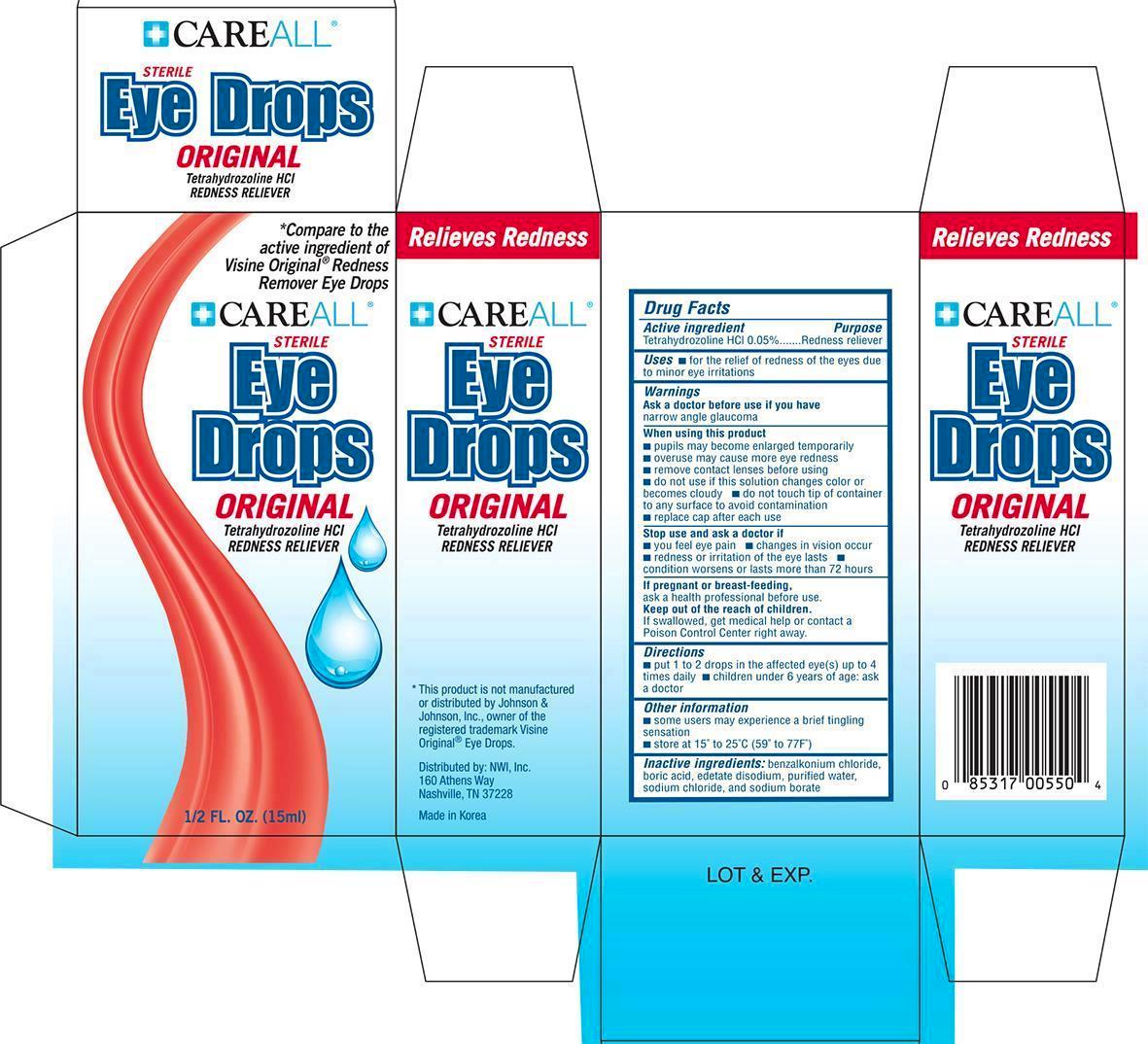 DRUG LABEL: CAREALL Eyedrops Original
NDC: 51824-039 | Form: SOLUTION/ DROPS
Manufacturer: New World Imports, Inc
Category: otc | Type: HUMAN OTC DRUG LABEL
Date: 20241007

ACTIVE INGREDIENTS: TETRAHYDROZOLINE HYDROCHLORIDE .5 mg/1 mL
INACTIVE INGREDIENTS: BENZALKONIUM CHLORIDE; BORIC ACID; EDETATE DISODIUM; WATER; SODIUM CHLORIDE; SODIUM BORATE

ACTIVE INGREDIENT

Tetrahydrozoline HCl 0.05%

PURPOSE

Redness Reliever

Keep out of reach of children. If swallowed, get medical help or contact a Poison Control Center right away

Use

For the relief of redness of the eye due to minor eye irritations

Ask a doctor before use if you have narrow angle glaucoma

When using this product

- pupils may become enlarged temporarily
- overuse may cause more eye redness
- remove contact lenses before using
- do not use if this solution changes color or becomes cloudy
- do not touch the tip of container to any surface to avoid contamination
- replace cap after each use

Stop use and ask a doctor if

- you feel eye pain
- changes in vision occur
- redness or irritation of the eyes last
- condition worsens or lasts more than 72 hours

If pregnant or breast feeding, ask a health professional before use.

DOSAGE AND ADMINISTRATION

Put 1 to 2 drops in the effected eye(s) up to 4 times daily.

Children under 6 years of age: ask a doctor

INACTIVE INGREDIENT

benzalkonium chloride, boric acid, edetate disodium, purified water, sodium chloride, sodium borate

QUESTIONS

Distributed by: NWI, Inc. 160 Athens Way. Nashville, TN 37228

(615)329-1906